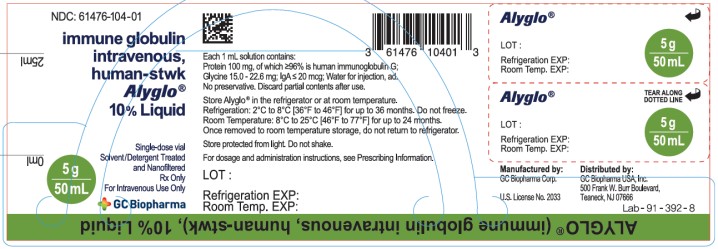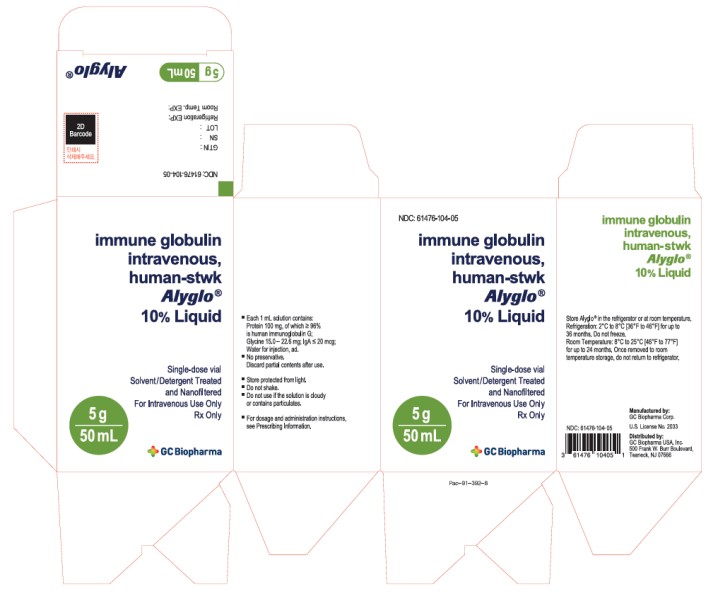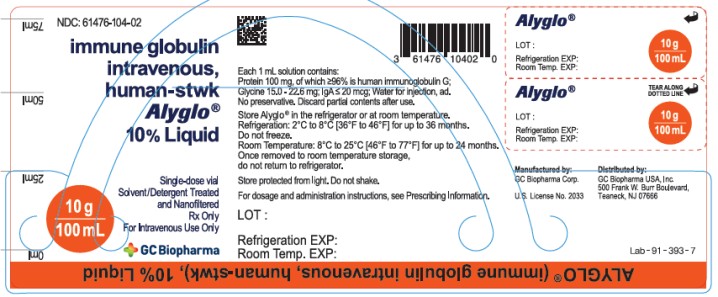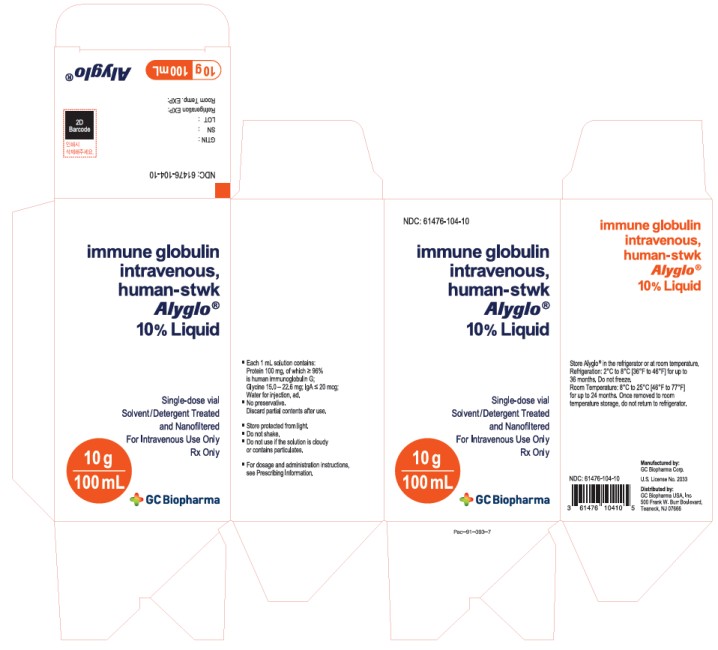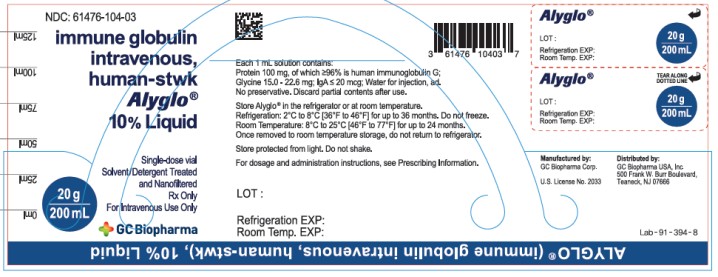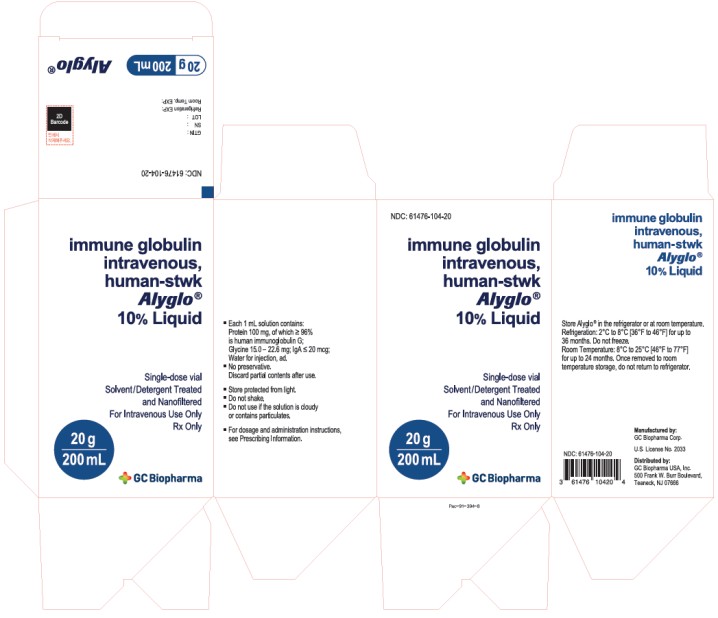 DRUG LABEL: Alyglo
NDC: 61476-104 | Form: LIQUID
Manufacturer: GC Biopharma Corp.
Category: other | Type: PLASMA DERIVATIVE
Date: 20250611

ACTIVE INGREDIENTS: Human immunoglobulin G 100 mg/1 mL
INACTIVE INGREDIENTS: Glycine; Water

HIGHLIGHTS OF PRESCRIBING INFORMATION

These highlights do not include all the information needed to use ALYGLO safely and effectively. See full prescribing information for ALYGLO.
ALYGLO (immune globulin intravenous, human-stwk), 10% Liquid
Initial U.S. Approval: 2023

WARNING: THROMBOSIS, RENAL DYSFUNCTION, AND ACUTE RENAL FAILURE

WARNING: THROMBOSIS, RENAL DYSFUNCTION AND
ACUTE RENAL FAILURE

See full prescribing information for complete boxed warning.

- Thrombosis may occur with immune globulin intravenous (IGIV) products, including ALYGLO. Risk factors may include: advanced age, prolonged immobilization, hypercoagulable conditions, history of venous or arterial thrombosis, use of estrogens, indwelling vascular catheters, hyperviscosity, and cardiovascular risk factors.
- Renal dysfunction, acute renal failure, osmotic nephropathy, and death may occur with the administration of IGIV products in predisposed patients.
- Renal dysfunction and acute renal failure occur more commonly in patients receiving IGIV products containing sucrose. ALYGLO does not contain sucrose.
- For patients at risk of thrombosis, renal dysfunction or renal failure, administer ALYGLO at the minimum dose and infusion rate practicable. Ensure adequate hydration in patients before administration. Monitor for signs and symptoms of thrombosis and assess blood viscosity in patients at risk for hyperviscosity.

1 INDICATIONS AND USAGE

ALYGLO (immune globulin intravenous, human-stwk) is a 10% immune globulin liquid for intravenous injection, indicated for the treatment of primary humoral immunodeficiency (PI) in adults (1).

2 DOSAGE AND ADMINISTRATION

For intravenous use only.

Dose | Infusion Number | Initial Infusion Rate | Maintenance Infusion Rate
300 ‒ 800 mg/kg body weight every 21 or 28 days | For the 1st Infusion | 1 mg/kg/min (0.01 mL/kg/min) | Double the infusion rate every 30 minutes (if tolerated) up to 8 mg/kg/min (0.08 mL/kg/min)
300 ‒ 800 mg/kg body weight every 21 or 28 days | From the 2nd Infusion | 2 mg/kg/min (0.02 mL/kg/min) | Double the infusion rate every 15 minutes (if tolerated) up to 8 mg/kg/min (0.08 mL/kg/min)

- Ensure that patients with pre-existing renal insufficiency are not volume-depleted; discontinue ALYGLO if renal function deteriorates (2.3, 5.3).
- For patients at risk of renal dysfunction or thrombotic events, administer ALYGLO at the minimum dose and infusion rate practicable (5.2, 5.3).

3 DOSAGE FORMS AND STRENGTHS

ALYGLO is a liquid solution containing 10% IgG (100 mg/mL) for intravenous infusion (3).

4 CONTRAINDICATIONS

- History of anaphylactic or severe systemic reactions to human immunoglobulin (4).
- IgA-deficient patients with antibodies against IgA or a history of hypersensitivity (4).

5 WARNINGS AND PRECAUTIONS

- IgA-deficient patients with antibodies to IgA are at greater risk of developing severe hypersensitivity and anaphylactic reactions to ALYGLO. Epinephrine should be available immediately to treat any severe acute hypersensitivity reactions (5.1).
- Thrombotic events have occurred in patients receiving IGIV treatments. Monitor patients with known risk factors for thrombotic events; consider baseline assessment of blood viscosity for patients at risk of hyperviscosity (5.2, 5.4).
- Monitor renal function, including blood urea nitrogen and serum creatinine, and urine output in patients at risk of developing acute renal failure (5.3).
- Hyperproteinemia, increased serum viscosity, and hyponatremia or pseudohyponatremia may occur in patients receiving IGIV therapy (5.4).
- Aseptic meningitis syndrome (AMS) may occur, especially with high doses or rapid infusion (5.5).
- Hemolysis that is either intravascular or due to enhanced red blood cell sequestration can develop subsequent to IGIV treatments. Risk factors for hemolysis include high doses and non-O blood group. Closely monitor patients for hemolysis and hemolytic anemia (5.6).
- Monitor patients for pulmonary adverse reactions [transfusion-related acute lung injury (TRALI)] (5.7).
- ALYGLO is made from human plasma and may contain infectious agents, e.g., viruses and, theoretically, the Creutzfeldt-Jakob disease (CJD) agent (5.8).

6 ADVERSE REACTIONS

The most common adverse reactions, observed in ≥ 5% of study subjects, were headache, nausea/vomiting, fatigue, nasal/sinus congestion, rash, arthralgia, diarrhea, muscle pain/aches, infusion site pain/swelling, abdominal pain/discomfort, cough, and dizziness(6).

To report SUSPECTED ADVERSE REACTIONS, contact GC Biopharma USA, Inc. at 1-833-426-6426 or FDA at 1-800-FDA-1088 or http://www.fda.gov/medwatch.

7 DRUG INTERACTIONS

- Passive transfer of antibodies may transiently interfere with the immune response to live virus vaccines, such as measles, mumps, and rubella (7).
- Passive transfer of antibodies may lead to misinterpretation of serological testing (7).

8 USE IN SPECIFIC POPULATIONS

- Geriatric use: In patients over age 65 or in any patient at risk of developing renal insufficiency, do not exceed the recommended dose, and infuse ALYGLO at the minimum infusion rate practicable (8.5).

FULL PRESCRIBING INFORMATION

WARNING: THROMBOSIS, RENAL DYSFUNCTION, AND ACUTE RENAL FAILURE

- Thrombosis may occur with immune globulin (IGIV) products, including ALYGLO. Risk factors may include: advanced age, prolonged immobilization, hypercoagulable conditions, history of venous or arterial thrombosis, use of estrogens, indwelling central vascular catheters, hyperviscosity, and cardiovascular risk factors. Thrombosis may occur in the absence of known risk factors [see Warnings and Precautions (5.2), Patient Counseling Information (17)].
- Renal dysfunction, acute renal failure, osmotic nephrosis, and death may occur in predisposed patients who receive IGIV products, including ALYGLO. Patients predisposed to renal dysfunction include those with any degree of pre-existing renal insufficiency, diabetes mellitus, age greater than 65, volume depletion, sepsis, paraproteinemia, or patients receiving known nephrotoxic drugs. Renal dysfunction and acute renal failure occur more commonly in patients receiving IGIV products containing sucrose. ALYGLO does not contain sucrose.
- For patients at risk of thrombosis, renal dysfunction or acute renal failure, administer ALYGLO at the minimum dose and infusion rate practicable. Ensure adequate hydration in patients before administration. Monitor for signs and symptoms of thrombosis and assess blood viscosity in patients at risk for hyperviscosity [see Dosage and Administration (2.3), Warnings and Precautions (5.3, 5.4)].

1 INDICATIONS AND USAGE

ALYGLO (immune globulin intravenous, human-stwk) is a 10% immune globulin liquid for intravenous injection, indicated for the treatment of primary humoral immunodeficiency (PI) in adults. This includes, but is not limited to, the humoral immune defect in congenital agammaglobulinemia, common variable immunodeficiency (CVID), X-linked agammaglobulinemia, Wiskott-Aldrich syndrome, and severe combined immunodeficiency (SCID).

2 DOSAGE AND ADMINISTRATION

For intravenous use only.

2.1 Dose

Table 1 Recommended Dose
Dose | Infusion Number | Initial Infusion Rate | Maintenance Infusion Rate
300 ‒ 800 mg/kg body weight every 21 or 28 days | For the 1st Infusion | 1 mg/kg/min (0.01 mL/kg/min) | Double the infusion rate every 30 minutes (if tolerated) up to 8 mg/kg/min (0.08 mL/kg/min)
300 ‒ 800 mg/kg body weight every 21 or 28 days | From the 2nd Infusion | 2 mg/kg/min (0.02 mL/kg/min) | Double the infusion rate every 15 minutes (if tolerated) up to 8 mg/kg/min (0.08 mL/kg/min)

Significant differences in the half-life of IgG among patients with PI may necessitate the dose and frequency of immunoglobulin therapy to vary from patient to patient. Determine the proper dose and frequency by monitoring clinical response.

Measles Exposure

If a patient has been exposed to measles, consult with physician to administer an extra dose of IGIV as soon as possible and within 6 days of exposure. A dose of 400 mg/kg should provide a serum level > 240 mIU/mL of measles antibodies for at least two weeks.

If a patient is at risk of future measles exposure and receives a dose of less than 530 mg/kg every 3 - 4 weeks, then the dose should be increased to at least 530 mg/kg. This should provide a serum level of 240 mIU/mL of measles antibodies for at least 22 days after infusion.

2.2 Preparation and Handling

- ALYGLO (immune globulin intravenous, human-stwk) is a clear or slightly opalescent, colorless or pale yellow solution. Inspect parenteral products visually for particulate matter and discoloration prior to administration, whenever solution and container permit. Do not use ALYGLO if the solution is cloudy or turbid, or if it contains particulate matter.
- Do not freeze, and do not use any ALYGLO that has been frozen.
- Do not shake.
- Do not mix ALYGLO with other IGIV products or other intravenous medications.
- Do not dilute.
- ALYGLO should be at room temperature at the time of administration. Allow refrigerated product to come to room temperature before use.
- Do not use beyond the expiration date on the product label.
- ALYGLO vial is for single use only. Due to the absence of anti-microbial preservatives, promptly administer ALYGLO after piercing the cap. Dispose of partially used or unused product.
- Infuse ALYGLO using a separate infusion line.
- An infusion pump may be used to control the rate of administration.
- ALYGLO may be pooled under aseptic conditions into sterile infusion bags. Infuse within 24 hours after pooling.

2.3 Administration

- Monitor vital signs throughout the infusion. Slow or stop the infusion if adverse reactions occur. If symptoms subside, the infusion may be resumed at a lower rate that is comfortable for the patient.
- Ensure that patients with pre-existing renal insufficiency are not volume-depleted. For patients at increased risk of renal dysfunction or thrombotic events, administer ALYGLO at the minimum infusion rate practicable, and consider discontinuation of administration if renal function deteriorates [see Boxed Warning, Warnings and Precautions (5.2, 5.3)].
- After administration, the infusion line may be flushed with either normal saline or 5% dextrose in water.

3 DOSAGE FORMS AND STRENGTHS

ALYGLO (immune globulin intravenous, human-stwk) is a liquid solution containing 10% IgG (100 mg/mL) for intravenous infusion.

4 CONTRAINDICATIONS

ALYGLO (immune globulin intravenous, human-stwk) is contraindicated in:

- Patients who have a history of anaphylactic or severe systemic reaction to the administration of human immune globulin.
- IgA-deficient patients with antibodies to IgA and a history of hypersensitivity [see Warnings and Precautions (5.1)].

5 WARNINGS AND PRECAUTIONS

5.1 Hypersensitivity

Severe hypersensitivity reactions may occur^1. In case of hypersensitivity, discontinue ALYGLO infusion immediately and institute appropriate treatment. Have epinephrine available for immediate treatment of severe acute hypersensitivity reactions.

ALYGLO contains trace amounts of IgA (≤ 20 mcg/mL) [see Description (11)]. Patients with known antibodies to IgA may have a greater risk of developing potentially severe hypersensitivity and anaphylactic reactions. ALYGLO is contraindicated in IgA-deficient patients with antibodies against IgA or a history of hypersensitivity reaction [see Contraindications (4)].

5.2 Thrombotic Events

Thrombosis may occur following treatment with ALYGLO^2,^3,^4. Risk factors may include: advanced age, prolonged immobilization, hypercoagulable conditions, history of venous or arterial thrombosis, use of estrogens, indwelling central vascular catheters, hyperviscosity and cardiovascular risk factors. Thrombosis may occur in the absence of known risk factors.

Consider baseline assessment of blood viscosity in patients at risk for hyperviscosity, including patients with cryoglobulins, fasting chylomicronemia/markedly high triacylglycerols (triglycerides), or monoclonal gammopathies. For patients at risk of thrombosis, administer ALYGLO at the minimum dose and infusion rate practicable. Ensure adequate hydration in patients before administration. Monitor for signs and symptoms of thrombosis and assess blood viscosity in patients at risk for hyperviscosity [see Boxed Warning, Dosage and Administration (2), Patient Counseling Information (17)].

5.3 Renal Failure

Renal dysfunction, acute renal failure, osmotic nephropathy, and death5 may occur upon use of ALYGLO. Ensure that patients are not volume-depleted before administering ALYGLO. Monitor renal function and urine output periodically, especially in patients who are at higher risk of renal failure. Assess renal function, including measurement of blood urea nitrogen (BUN) and serum creatinine before the initial infusion of ALYGLO and at appropriate intervals thereafter. If renal function deteriorates, consider discontinuing ALYGLO [see Patient Counseling Information (17)]. In patients who are at risk of developing renal dysfunction, because of pre-existing renal insufficiency or predisposition to acute renal failure (such as diabetes mellitus, hypovolemia, overweight, use of concomitant nephrotoxic medicinal products or age > 65 years), administer ALYGLO at the minimum infusion rate practicable [see Boxed Warning, Dosage and Administration (2)].

5.4 Hyperproteinemia, Increased Serum Viscosity, and Hyponatremia

Hyperproteinemia, increased serum viscosity, and hyponatremia may occur in patients receiving ALYGLO. It is critical to clinically distinguish true hyponatremia from a pseudohyponatremia that is associated with or causally related to hyperproteinemia with concomitant decreased calculated serum osmolality or elevated osmolar gap. Such treatment aimed at decreasing serum free water in patients with pseudohyponatremia may lead to volume depletion, a further increase in serum viscosity, and a possible predisposition to thrombotic events^6.

5.5 Aseptic Meningitis Syndrome (AMS)

AMS may occur with ALYGLO. AMS usually begins within several hours to 2 days following ALYGLO treatment. Discontinuation of treatment has resulted in remission of AMS within several days without sequelae^7,^8,^9.

AMS may occur more frequently with high doses (2 g/kg) and/or rapid infusion of ALYGLO. AMS is characterized by the following signs and symptoms: Severe headache, nuchal rigidity, drowsiness, fever, photophobia, painful eye movements, nausea, and vomiting [see Patient Counseling Information (17)]. Cerebrospinal fluid (CSF) studies frequently reveal pleocytosis up to several thousand cells per cubic millimeter, predominantly from the granulocytic series, and elevated protein levels up to several hundred mg/dL, but negative culture results. Conduct a thorough neurological examination on patients exhibiting such signs and symptoms, including CSF studies, to rule out other causes of meningitis.

5.6 Hemolysis

ALYGLO may contain blood group antibodies that can act as hemolysins and induce in vivo coating of red blood cells (RBCs) with immunoglobulin, causing a positive direct antiglobulin test (DAT) (Coombs test) result and hemolysis^10,^11,^12. Delayed hemolytic anemia due to enhanced RBC sequestration, and acute hemolysis, consistent with intravascular hemolysis, have been reported. Cases of severe hemolysis-related renal dysfunction/failure or disseminated intravascular coagulation have occurred following infusion of IGIV.

The following risk factors may be associated with the development of hemolysis following IGIV administration: High doses (e.g., 2 g/kg or more), given either as a single administration or divided over several days, and non-O blood group^13. Other individual patient factors, such as an underlying inflammatory state (as may be reflected by, for example, elevated C-reactive protein or erythrocyte sedimentation rate), have been hypothesized to increase the risk of hemolysis following administration of IGIV^14, but their role is uncertain.

Closely monitor patients for clinical signs and symptoms of hemolysis, particularly patients with risk factors noted above. Consider appropriate laboratory testing in higher risk patients, including measurement of hemoglobin or hematocrit.

If clinical signs and symptoms of hemolysis or a significant drop in hemoglobin or hematocrit have been observed, perform confirmatory laboratory testing, including direct antiglobulin test. If transfusion is indicated for patients who develop hemolysis with clinically compromising anemia after receiving ALYGLO, perform adequate cross-matching to avoid exacerbating ongoing hemolysis.

5.7 Transfusion-Related Acute Lung Injury (TRALI)

Noncardiogenic pulmonary edema [Transfusion-Related Acute Lung Injury (TRALI)] may occur in patients administered ALYGLO^15. TRALI is characterized by severe respiratory distress, pulmonary edema, hypoxemia, normal left ventricular function, and fever. Signs and symptoms typically appear within 1 to 6 hours following treatment. Patients with TRALI may be managed using oxygen therapy with adequate ventilator support.

Monitor patients for pulmonary adverse reactions. If TRALI is suspected, perform appropriate tests for the presence of anti-neutrophil antibodies and anti-human leukocyte antigen (HLA) antibodies in both the product and the patient's serum.

5.8 Transmissible Infectious Agents

Because ALYGLO is made from human blood, it may carry a risk of transmitting infectious agents, e.g., viruses, the variant Creutzfeldt-Jakob disease (vCJD) agent and, theoretically, the Creutzfeldt-Jakob disease (CJD) agent. The risk of infectious agent transmission has been reduced by screening plasma donors and by including virus inactivation/removal steps in the manufacturing process of ALYGLO.

Report all infections thought by a physician possibly transmitted by ALYGLO to GC Biopharma USA, Inc. at 1-833-426-6426. Discuss the risks and benefits of its use with the patient before prescribing or administering this product [see Patient Counseling Information (17)].

5.9 Monitoring Laboratory Tests

- Periodic monitoring of renal function and urine output is particularly important in patients at increased risk of developing acute renal failure. Assess renal function, including measurement of blood urea nitrogen (BUN) and serum creatinine before the initial infusion of ALYGLO and at appropriate intervals thereafter.
- Because of the potential for increased risk of thrombosis with ALYGLO, consider baseline assessment of blood viscosity in patients at risk for hyperviscosity, including those with cryoglobulins, fasting chylomicronemia/markedly high triacylglycerols (triglycerides), or monoclonal gammopathies.
- If signs and/or symptoms of hemolysis are present after an infusion of ALYGLO, perform appropriate laboratory testing for confirmation. Measure hemoglobin and/ or hematocrit at baseline and approximately 36 to 96 hours post-infusion in patients at higher risk of hemolysis.
- If TRALI is suspected, perform appropriate tests for the presence of anti-neutrophil antibodies in both the product and patient's serum.

5.10 Interference with Laboratory Tests

After infusion of immunoglobulin, the transitory rise of the various passively transferred antibodies in the patient's blood may yield positive serological testing results, with the potential for misleading interpretation. Passive transmission of antibodies to erythrocyte antigens (e.g., A, B, and D) may cause a positive direct or indirect antiglobulin (Coombs) test.

6 ADVERSE REACTIONS

The most common adverse reactions, observed in ≥ 5% of study subjects, were headache, nausea/vomiting, fatigue, nasal/sinus congestion, rash, arthralgia, diarrhea, muscle pain/aches, infusion site pain/swelling, abdominal pain/discomfort, cough, and dizziness.

6.1 Clinical Trials Experience

Because clinical trials are conducted under widely varying conditions, adverse reaction rates observed in the clinical trials of a drug cannot be directly compared to rates in the clinical trials of another drug and may not reflect the rates observed in practice.

In an open-label, single-arm, multicenter, non-randomized clinical trial, 33 subjects with primary humoral immunodeficiency received doses of ALYGLO (immune globulin intravenous, human-stwk) ranging from 319 mg/kg to 817 mg/kg every 21 days or 28 days for up to 12 months.

Twenty-eight subjects (85%) experienced a total of 145 temporally associated adverse reactions (adverse events that occurred during or within 72 hours after the end of an infusion) during the study. The temporally associated ARs were headache (13 subjects, 39%), nausea/vomiting (11 subjects, 33%), fatigue (6 subjects, 18%), nasal/sinus congestion (5 subjects, 15%), rash (4 subjects, 12%), arthralgia, diarrhea (3 subjects, 9% each), muscle pain/aches, Infusion site pain/swelling, abdominal pain/discomfort, cough, dizziness (2 subjects, 6% each). These are presented in Table 2.

There were no deaths and no adverse reactions leading to withdrawal from the study.

Table 2 Adverse Reactions* (ARs) (within 72 hours after the end of an ALYGLO infusion) in ≥ 5% of Subjects
Adverse Reactions (ARs) | No. of Subjects Reporting ARs (Percentage of Subjects) [N^1=33] | No. of Infusions with ARs (Percentage of Infusions) [N^2=427]
Headache | 13 (39) | 32 (7.5)
Nausea/vomiting | 11 (33) | 20 (4.7)
Fatigue | 6 (18) | 18 (4.2)
Nasal/sinus congestion | 5 (15) | 5 (1.2)
Rash | 4 (12) | 4 (0.9)
Arthralgia | 3 (9) | 4 (0.9)
Diarrhea | 3 (9) | 3 (0.7)
Muscle pain/aches | 2 (6) | 7 (1.6)
Infusion site pain/swelling | 2 (6) | 6 (1.4)
Abdominal pain/discomfort | 2 (6) | 3 (0.7)
Cough | 2 (6) | 2 (0.5)
Dizziness | 2 (6) | 2 (0.5)

* Adverse events that occurred during or within 72 hours after the end of an infusion

^1 Total number of subjects

^2 Total number of infusions

6.2 Postmarketing Experience

Because postmarketing reporting of adverse reactions is voluntary and from a population of uncertain size, it is not always possible to reliably estimate the frequency of these reactions or establish a causal relationship to product exposure. The following adverse reactions have been identified and reported during the post-approval use of marketed IGIV products:

Blood and lymphatic system disorders
Leucopenia, hemolysis, pancytopenia

Immune system disorders
Hypersensitivity (e.g., anaphylaxis), anaphylactic shock, anaphylactic reaction, anaphylactoid reaction, allergic reaction, angioedema, face edema

Metabolic and nutritional disorders
Fluid overload, (pseudo) hyponatremia

Psychiatric disorders
Agitation, confusion, anxiety, nervousness

Nervous system disorders
Coma, loss of consciousness, seizures, (acute) encephalopathy, cerebrovascular accident, stroke, aseptic meningitis, migraine, speech disorder, paresthesia, hypoesthesia, photophobia, tremor

Cardiac disorders
Myocardial infarction, cardiac arrest, angina pectoris, tachycardia, bradycardia, palpitations, cyanosis

Vascular disorders
Hypotension, (deep vein) thrombosis, peripheral circulatory failure/collapse, hypertension, phlebitis, pallor

Respiratory, thoracic and mediastinal disorders
Apnea, Acute Respiratory Distress Syndrome (ARDS), TRALI, respiratory failure, pulmonary embolism, pulmonary edema, bronchospasm, dyspnea, hypoxia, wheezing, cough

Gastrointestinal disorders
Diarrhea, hepatic dysfunction, abdominal discomfort

Skin and subcutaneous tissue disorders
Eczema, urticaria, rash (erythematous), dermatitis, pruritus, alopecia, Stevens-Johnson syndrome, epidermolysis, skin exfoliation, erythema (multiform), dermatitis (e.g., bullous dermatitis)

Musculoskeletal and connective tissue disorders
Back pain, arthralgia, myalgia, musculoskeletal pain, muscle stiffness, pain in extremity, neck pain, muscle spasm

Renal and urinary disorders
Acute renal failure, osmotic nephropathy, renal pain

General disorders and administration site conditions
Injection-site reaction, chills, chest pain or discomfort, hot flush, flushing, flu-like illness, feeling cold or hot, edema, hyperhidrosis, malaise, asthenia, lethargy, burning sensation

Investigations
Hepatic enzymes increased, oxygen saturation decreased, falsely elevated erythrocyte sedimentation rate, positive direct antiglobulin (Coombs) test

7 DRUG INTERACTIONS

Clinical studies have not evaluated mixture of ALYGLO (immune globulin intravenous, human-stwk) with other drugs and intravenous solutions. It is recommended that ALYGLO is administered separately from other drugs or medications which the patient may be receiving. Do not mix the product.

Transitory rise of the various passively transferred antibodies in the patient's blood after infusion of immunoglobulin may yield positive serological testing results, with the potential for misleading interpretation. Passive transmission of antibodies to erythrocyte antigens (e.g., A, B, and D) may cause a positive direct or indirect antiglobulin (Coombs) test.

The passive transfer of antibodies with IGIV administration may interfere with the response to live virus vaccines such as measles, mumps, rubella, and varicella. Immunizing physicians should be informed of recent IGIV therapy so that appropriate measures may be taken. [See Patient Counseling Information (17)]

8 USE IN SPECIFIC POPULATIONS

8.1 Pregnancy

Risk Summary

No human data are available to indicate the presence or absence of drug-associated risk. Animal reproduction studies have not been conducted with ALYGLO (immune globulin intravenous, human-stwk). It is not known whether ALYGLO can cause fetal harm when administered to a pregnant woman or can affect reproduction capacity. Immune globulins cross the placenta from maternal circulation increasingly after 30 weeks of gestation. In the U.S. general population, the estimated background risk of major birth defects and miscarriage in clinically recognized pregnancies is 2 – 4% and 15 – 20%, respectively16,17. ALYGLO should be given to pregnant women only if clearly needed.

8.2 Lactation

Risk Summary

No human data are available to indicate the presence or absence of drug-associated risk during lactation. The developmental and health benefits of breastfeeding should be considered along with the mother's clinical need for ALYGLO and any potential adverse effects on the breastfed infant from ALYGLO or from the underlying maternal condition.

8.4 Pediatric Use

Safety and effectiveness in pediatric patients < 17 years has not been established.

8.5 Geriatric Use

Clinical studies of ALYGLO did not include sufficient numbers of subjects aged 65 and over to determine whether they respond differently from younger subjects. Other reported clinical experience has not identified differences in responses between the elderly and younger patients. In general, dose selection for an elderly patient should be cautious, usually starting at the low end of the dosing range, reflecting the greater frequency of decreased hepatic, renal, or cardiac function, and of concomitant disease or other drug therapy.

10 OVERDOSAGE

Overdosage may lead to fluid overload and hyperviscosity. Patients at risk of complications of fluid overload and hyperviscosity include elderly patients and those with cardiac or renal impairment.

11 DESCRIPTION

ALYGLO (immune globulin intravenous, human-stwk) is a ready-to-use, sterile, liquid preparation of highly purified and concentrated human immunoglobulin G (IgG) antibodies. The product is a clear or slightly opalescent liquid, which is colorless or pale yellow. The distribution of the IgG subclasses is similar to that of normal human plasma. The active ingredient is human immunoglobulin G purified from human Source Plasma and processed using a modified Cohn-Oncley fractionation process, as well as anion and cation exchange chromatography.

ALYGLO contains 100 mg/mL protein, of which not less than ≥ 96% is human IgG obtained from human Source Plasma. It is formulated with glycine targeted at 18.8 mg/mL (15.0 – 22.6 mg/mL) as a stabilizer and water for injection as a solvent with pH in the range of 4.5 – 5.5. ALYGLO contains ≤ 20 mcg/mL of IgA. The osmolality is in the range of 240-360 mOsmol/kg, which is similar to physiological osmolality (average 275 to 295 mOsmol/kg). There are no added sugars, sodium or preservatives.

All plasma units used in the manufacture of ALYGLO have been tested and approved for manufacture using FDA-licensed serological assays for human hepatitis B surface antigen (HBsAg) and antibodies to human hepatitis C virus (anti-HCV) and human immunodeficiency virus types 1 and 2 (anti-HIV-1/2) as well as FDA-licensed Nucleic Acid Testing (NAT) for HIV-1, HAV, HBV, and HCV and found to be non-reactive (negative). In addition, the plasma has been tested for human parvovirus B19 by NAT. Only plasma that passed virus screening is used for production, and the limit for human parvovirus B19 in the manufacturing plasma pool is set not to exceed 10,000 IU/mL.

The manufacturing process for ALYGLO includes three steps to reduce the risk of virus transmission. The steps are “Fractionation I+III, solvent/detergent (S/D) treatment, and Nanofiltration.”

The steps of Fractionation I+III and Nanofiltration (20 nm) remove both enveloped and non-enveloped viruses, and the S/D treatment step inactivates enveloped viruses. The results of virus validation studies for ALYGLO are shown in Table 3, expressed as log^10 reduction factor (LRF).

Table 3 Summary of Virus Validation Study Results for ALYGLO
Manufacturing Step | LRF for HIV-1^1 | LRF for PRV^1 | LRF for BVDV^1 | LRF for EMCV^2 | LRF for PPV^2
Fractionation I+III | 4.27 | 3.53 | 3.00 | 2.95 | 4.28
S/D treatment | ≥ 5.51 | ≥ 4.43 | ≥ 4.63 | NT | NT
Nanofiltration | ≥ 4.77 | ≥ 4.45 | ≥ 5.67 | ≥ 5.20 | 3.65
Total LRF | ≥ 14.55 | ≥ 12.41 | ≥ 13.30 | ≥ 8.15 | 7.93

NT: Not Tested

^1 Enveloped viruses

^2 Non-enveloped viruses

HIV-1: Human Immunodeficiency virus type 1, a model for HIV-1 and HIV-2, PRV: Pseudorabies virus, a model for large enveloped DNA viruses (e.g., herpes virus); BVDV: Bovine viral diarrhea virus a model for e.g., Hepatitis C virus (HCV) and West Nile virus (WNV); EMCV: Encephalomyocarditis virus, a model for Hepatitis A virus (HAV); PPV: Porcine parvovirus, a model for Human Parvovirus B19

12 CLINICAL PHARMACOLOGY

12.1 Mechanism of Action

ALYGLO (immune globulin intravenous, human-stwk) supplies a broad spectrum of neutralizing IgG antibodies to bacterial and viral pathogens, and their toxins. The mechanism of action has not been fully elucidated in PI.

12.2 Pharmacodynamics

ALYGLO contains mainly IgG with a broad spectrum of antibodies against various infectious agents reflecting the IgG activity found in the donor population. ALYGLO which is prepared from pooled material, has an IgG subclass distribution similar to that of native human plasma. An adequate dose of IGIV can restore abnormally low IgG level to the normal range. Standard pharmacodynamics studies were not performed.

12.3 Pharmacokinetics

Serum concentrations of total IgG were measured in 22 subjects (22 adults aged ≥ 17 to 70 years) following the 5th infusion of ALYGLO. The administered dose of ALYGLO during the PK assessment ranged from 313 mg/kg to 821 mg/kg. Blood samples for PK analyses were collected until Day 22 (±1 day) or Day 29 (±2 days) for subjects treated according to the 21 days and 28 days schedule, respectively.

Table 4 summarizes the PK parameters of ALYGLO based on serum concentration of total IgG.

Table 4 Total IgG Pharmacokinetics of ALYGLO
Parameter (unit) | Statistics | 21 Days Schedule, Baseline Unadjusted (N=7) | 21 Days Schedule, Baseline Adjusted (N=7) | 28 Days Schedule, Baseline Unadjusted (N=15) | 28 Days Schedule, Baseline Adjusted (N=15)
Cmax (mg/mL) | Mean (SD) | 24.1 (4) | 14.4 (3) | 21.2 (4) | 13.5 (4)
AUC 0-tau (day×mg/mL) | Mean (SD) | 270.9 (56) | 79.3 (32) | 310.2 (61) | 96.6 (62)
T 1/2 (day) | Mean (SD) | 20.0 (6) | 7.1 (5) | 29.6 (11) | 6.0 (3)
Tmax (day) | Mean (SD) | 0.4 (1) | 0.4 (1) | 0.2 (0) | 0.2 (0)
CL (mL/day/kg) | Mean (SD) | 2.5 (1) | 9.2 (3) | 1.7 (0) | 8.1 (8)
Vss (mL/kg) | Mean (SD) | 63.0 (1) | 49.9 (13) | 48.2 (4) | 50.9 (20)

AUC0-tau=area under the (time concentration) curve within a dosing interval; CL=clearance based on AUC0-tau; Cmax=maximum serum concentration; SD=standard deviation; Tmax=time to maximum serum concentration; T1/2=elimination half-life; Vss=(apparent) volume of distribution at steady state based on AUC0-tau

13 NONCLINICAL TOXICOLOGY

13.1 Carcinogenesis, Mutagenesis, Impairment of Fertility

No animal studies were conducted on carcinogenesis, mutagenesis, or impairment of fertility with ALYGLO (immune globulin intravenous, human-stwk).

13.2 Animal Toxicology and/or Pharmacology

A single-dose toxicity study was performed in rats at doses up to 3000 mg/kg body weight. No toxicologically significant changes attributable to the test article were observed at any dose.

In safety pharmacology studies, there were no test article related adverse effects on respiratory, cardiovascular or central nervous systems of the treated mice and rats.

14 CLINICAL STUDIES

A prospective, open-label, single-arm, multi-center study was conducted in North America (the United States and Canada) to determine efficacy, safety and PK of ALYGLO (immune globulin intravenous, human-stwk) in adults and pediatric subjects with PI. Prior to enrollment, all subjects were receiving stable doses between 300 and 900 mg/kg of IGIV replacement therapy. Subjects received ALYGLO infusion administered every 21 or 28 days (both the dose and schedule depending on their prior therapy) for 12 months.

Thirty-three adults aged 17 to 70 years were enrolled and received doses ranging from 319 to 817 mg/kg. The age range was between 17 and 70 years, with a mean (SD) of 49.6 (16.41) years. Eighteen (54.5%) subjects were female and 15 (45.5%) subjects were male; 32 (97.0%) were White and 1 (3.0%) was other.

The primary efficacy analysis was annualized rate of acute serious bacterial infections (SBIs), defined as bacterial pneumonia, bacteremia/sepsis, bacterial meningitis, visceral abscess, and osteomyelitis/septic arthritis per subject per year. Secondary analyses were annual rate or days of other infections, antibiotic use, days out of work/school/day care or unable to perform normal activities due to infection, and days of hospitalization due to infection.

During the 12-month study period, the acute SBI rate was 0.03 (with an upper one-sided 99% confidence limit: 0.31), which met the predefined success rate of less than one acute SBI per subject per year (ITT Population). One adult subject experienced an acute SBI (one episode of bacterial pneumonia).

Table 5 summarizes the efficacy results for all 33 subjects.

Table 5 Summary of Efficacy Results in Adult Subjects with PI
Category | Result
Subject | 33 subjects with 30 subject years on study
Annual rate of confirmed acute SBIs | 0.03 acute SBIs/person-year
Annual rate of other infections | 2.4 infections/person-year
Number of subjects with use of therapeutic antibiotics | 19 subjects (58%)
Number of days of therapeutic antibiotics | 14 (5, 63) days*
Number of subjects missed at least one day from work/school or days unable to perform normal daily activities due to infection | 14 subjects (42%)
Number of days off work/school or days unable to perform normal daily activities due to infection | 6 (1, 80) days*
Number of subjects with at least one day of unscheduled physician visits | 19 subjects (58%)
Number of subjects with hospitalizations due to infection | 2 subjects (6%)
Total days of hospitalization due to infection | 5 days (One subject for 2 days and one subject for 3 days)
Annual rate of hospitalizations due to infection | 0.2 days/person-year

* Number of days is presented as median (min, max)

15 REFERENCES

1. Duhem C, Dicato MA, Ries F. Side-effects of intravenous immune globulins. Clin Exp Immunol 1994: 97 Suppl 1:79-83.
2. Dalakas MC. High-dose intravenous immunoglobulin and serum viscosity: risk of precipitating thromboembolic events. Neurology 1994; 44:223- 226.
3. Woodruff RK, Grigg AP, Firkin FC, Smith IL. Fatal thrombotic events during treatment of autoimmune thrombocytopenia with intravenous immunoglobulin in elderly patients. Lancet 1986; 2:217-218.
4. Wolberg AS, Kon RH, Monroe DM, Hoffman M. Coagulation factor XI is a contaminant in intravenous immunoglobulin preparations. Am J Hematol 2000; 65:30-34.
5. Cayco AV, Perazella MA, and Hayslett JP. Renal insufficiency after intravenous immune globulin therapy: a report of two cases and an analysis of the literature. J Am Soc Nephrol 1997; 8:1788-1794.
6. Steinberger BA, Ford SM, Coleman TA. Intravenous immunoglobulin therapy results in post-infusional hyperproteinemia, increased serum viscosity, and pseudohyponatremia. Am J Hematol 2003; 73:97-100.
7. Casteels-Van Daele M, et al. Intravenous immune globulin and acute aseptic meningitis [letter]. N Engl J Med 1990; 323:614-615.
8. Kato E, et al. Administration of immune globulin associated with aseptic meningitis [letter]. Jama 1988; 259:3269-3271.
9. Scribner CL, et al. Aseptic meningitis and intravenous immunoglobulin therapy [editorial, comment]. Ann Intern Med 1994; 121:305-306.
10. Copelan EA, Stohm PL, Kennedy MS, Tutschka PJ. Hemolysis following intravenous immune globulin therapy. Transfusion 1986; 26:410-412.
11. Thomas MJ, Misbah SA, Chapel HM, Jones M, Elrington G, Newsom-Davis J. Hemolysis after high-dose intravenous Ig. Blood 1993; 15:3789.
12. Wilson JR, Bhoopalam N, Fisher M. Hemolytic anemia associated with intravenous immunoglobulin. Muscle & Nerve 1997; 20:1142-1145.
13. Kahwaji J, Barker E, Pepkowitz S, et al. Acute Hemolysis After High-Dose Intravenous Immunoglobulin Therapy in Highly HLA Sensitized Patients. Clin J Am Soc Nephrol 2009;4:1993-1997.
14. Daw Z, Padmore R, Neurath D, et al. Hemolytic transfusion reactions after administration of intravenous immune (gamma) globulin: A case series analysis. Transfusion 2008;48:1598-1601.
15. Rizk A, Gorson KC, Kenney L, Weinstein R. Transfusion-related acute lung injury after the infusion of IVIG. Transfusion 2001; 41:264-268.
16. Hammarström L, Smith CIE. Placental transfer of intravenous immunoglobulin. Lancet 1986;1:681.
17. Sidiropoulos D, Herman U Jr, Morell A, von Muralt G, Barandun S. Transplacental passage of intravenous immunoglobulin in the last trimester of pregnancy. J Pediatr 1986;109:505-508.

16 HOW SUPPLIED/STORAGE AND HANDLING

ALYGLO (immune globulin intravenous, human-stwk) is supplied in single-dose, tamper-evident vial containing the labeled amount of functionally active IgG. The components used in the packaging for ALYGLO are not made with natural rubber latex.

The following presentations of ALYGLO are available.

Grams and Fill Size | Vial NDC Number | Carton NDC Number
5 g in 50 mL | 61476 -104-01 | 61476 -104-05
10 g in 100 mL | 61476 -104-02 | 61476 -104-10
20 g in 200 mL | 61476 -104-03 | 61476 -104-20

- Keep ALYGLO in its original carton to protect it from light.
- Store ALYGLO in the refrigerator or at room temperature.
- Refrigeration: 2°C to 8°C [36°F to 46°F] for up to 36 months. Do not freeze.
- Room Temperature: 8°C to 25°C [46°F to 77°F] for up to 24 months. Do not return to refrigeration after ALYGLO has been stored at room temperature.
- Expiration dates for both conditions are printed on the outer carton and vial label. Do not use after the expiration date.
- ALYGLO contains no preservatives. The ALYGLO bottle is for single use only. Use promptly any bottle that has been entered or opened and discard partially used bottles.
- Dispose of any unused product or waste material in accordance with local requirements.

17 PATIENT COUNSELING INFORMATION

Inform patients to immediately report the following signs and symptoms to their healthcare professional:

- Thrombosis which includes pain and/or swelling of an arm or legs/feet with warmth over the affected area, discoloration of an arm or leg, unexplained shortness of breath, acute chest pain or discomfort that worsens on deep breathing, unexplained rapid pulse, numbness or weakness on one side of the body [see Warning and Precaution (5.2)].
- Acute renal dysfunction and acute renal failure which includes decreased urine output, sudden weight gain, fluid retention/edema, and/or shortness of breath. Such symptoms may suggest kidney damage [see Boxed Warning, Warnings and Precautions (5.3)].
- Aseptic meningitis syndrome (AMS) which includes severe headache, neck stiffness, drowsiness, fever, sensitivity to light, painful eye movements, nausea and vomiting [see Warnings and Precautions (5.5)].
- Hemolysis which includes fatigue, increased heart rate, yellowing of skin or eyes, dark-colored urine [see Warnings and Precautions (5.6)].
- Transfusion-Related Acute Lung Injury (TRALI) which includes trouble breathing, chest pain, blue lips or extremities, fever [see Warnings and Precautions (5.7)].

Inform patients that ALYGLO (immune globulin intravenous, human-stwk) is made from human plasma and may contain infectious agents that can cause disease. While the risk that ALYGLO can transmit an infection has been reduced by screening plasma donors for prior exposure, testing donated plasma, and inactivating or removing certain viruses during manufacturing, patients should report any symptoms that concern them [see Warnings and Precautions (5.8)].

Inform patients that ALYGLO can interfere with their immune response to live viral vaccines (e.g., measles, mumps, and rubella), and instruct patients to notify their healthcare professional of this potential interaction when they are receiving vaccinations [see Drug Interaction (7)].

Manufactured by:

GC Biopharma Corp.
107 Ihyeon-ro 30-beongil,
Giheung-gu, Yongin-si,
Gyeonggi-do 16924,
Republic of Korea

U.S. License No. 2033

Distributed by:

GC Biopharma USA, Inc.
500 Frank W. Burr Boulevard,
Teaneck, NJ 07666, USA

PRINCIPAL DISPLAY PANEL

NDC 61476-104-01
immune globulin intravenous,
human-stwk)
ALYGLO
10% Liquid

PRINCIPAL DISPLAY PANEL

NDC 61476-104-05
immune globulin intravenous,
human-stwk)
ALYGLO
10% Liquid

PRINCIPAL DISPLAY PANEL

NDC 61476-104-02
immune globulin intravenous,
human-stwk)
ALYGLO
10% Liquid

PRINCIPAL DISPLAY PANEL

NDC 61476-104-10
immune globulin intravenous,
human-stwk)
ALYGLO
10% Liquid

PRINCIPAL DISPLAY PANEL

NDC 61476-104-03
immune globulin intravenous,
human-stwk)
ALYGLO
10% Liquid

PRINCIPAL DISPLAY PANEL

NDC 61476-104-20
immune globulin intravenous,
human-stwk)
ALYGLO
10% Liquid